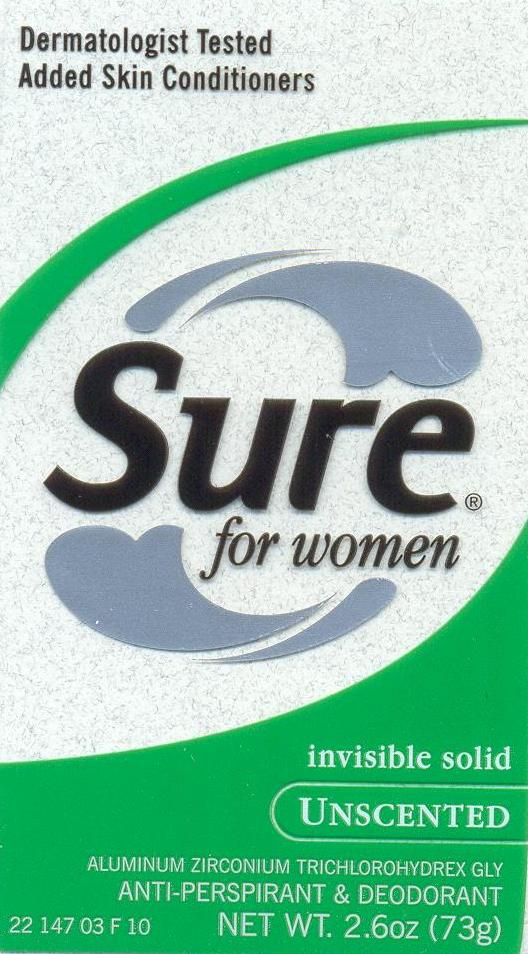 DRUG LABEL: Sure
NDC: 41595-5537 | Form: STICK
Manufacturer: Innovative Brands, LLC
Category: otc | Type: HUMAN OTC DRUG LABEL
Date: 20091210

ACTIVE INGREDIENTS: ALUMINUM ZIRCONIUM TRICHLOROHYDREX GLY 19 g/100 g
INACTIVE INGREDIENTS: CYCLOMETHICONE 5; Stearyl Alcohol; Petrolatum; Dimethicone; Hydrogenated Castor Oil; Talc; Mineral oil; Docosanol; LOW DENSITY POLYETHYLENE; ALOE VERA LEAF; VITAMIN A PALMITATE; .ALPHA.-TOCOPHEROL ACETATE, DL-

PACKAGE LABEL

Sure for Women Invisible Solid Unscented
MM1

Active Ingredient

Aluminum Zirconium Trichlorohydrex GLY 19% (anhydrous)

Purpose and Uses

Purpose

Antiperspirant

Use

Reduces underarm wetness

Warnings

For external use only.

Do not use on broken skin

Ask a doctor before use if you have kidney disease

Stop use

Stop use if rash or irritation occurs

Keep out of reach of children. If swallowed, get medical help or contact a Poison Control Center right away.

Directions

Apply to underarms only

Inactive Ingredients

Cyclopentasiloxane, Stearyl Alcohol, Dimethicone, Petrolatum, PPG-14 Butyl Ether, Hydrogenated Castor Oil, Talc, Fragrance, Retinyl Palmitate (Vitamin A), Tocopherol, Tocopheryl Acetate (Vitamin E), Mineral Oil, Aloe Barbadensis Leaf Extract, Behenyl Alcohol

Questions

www.sureap.com

1-800-944-4477

Distributed by Innovative Brands, LLC

under license from Procter and Gamble.

Phoenix, AZ 85050

Made in Canada